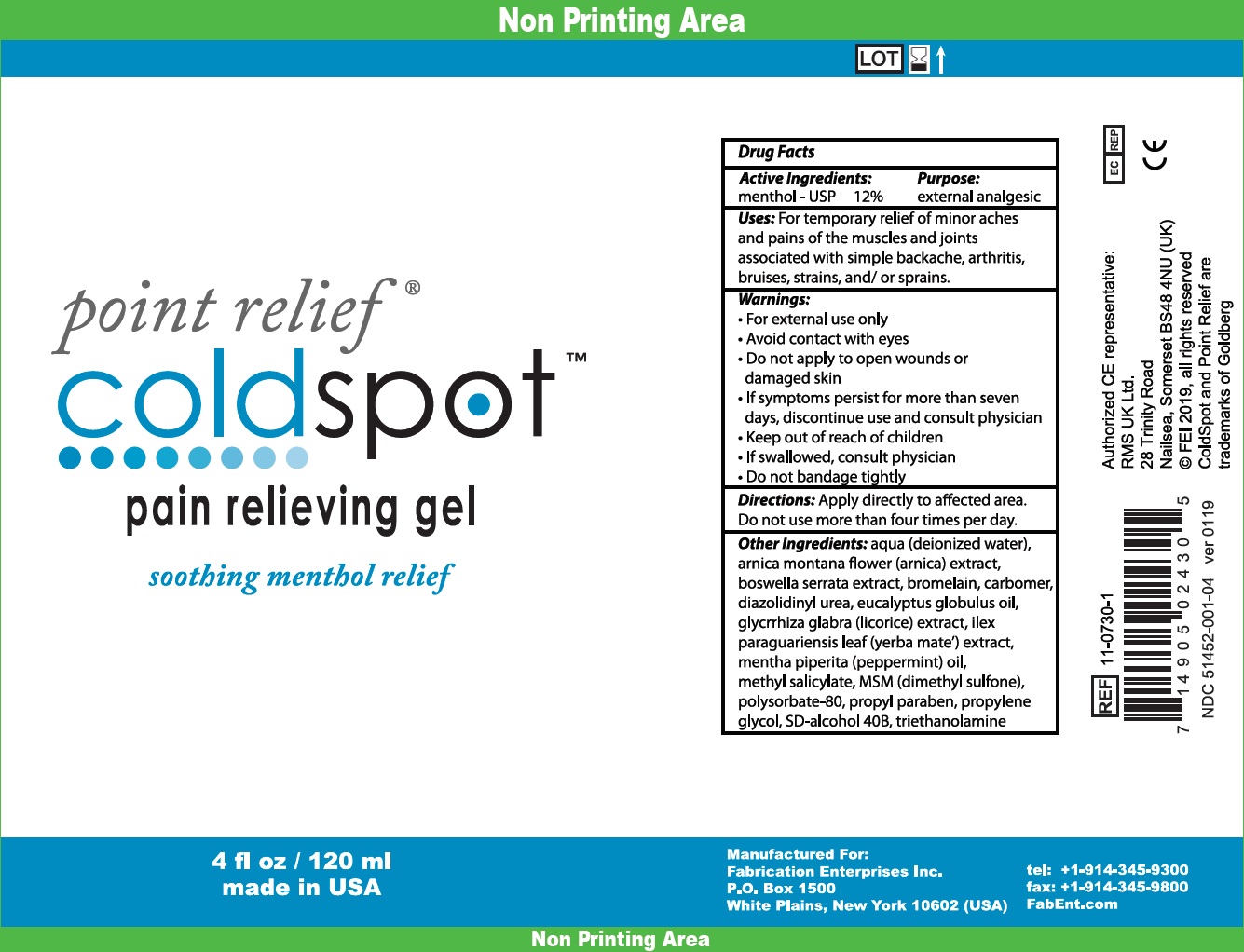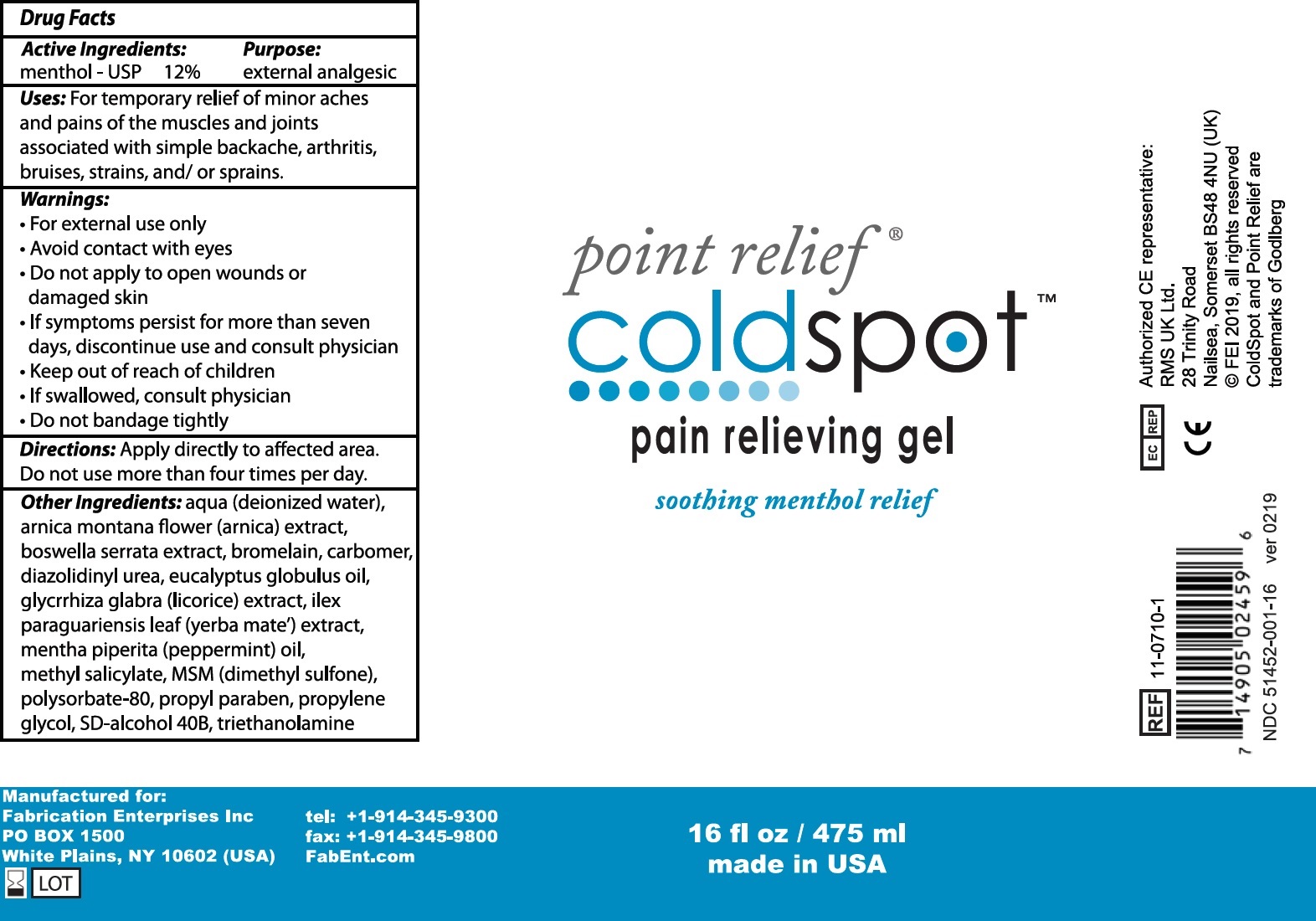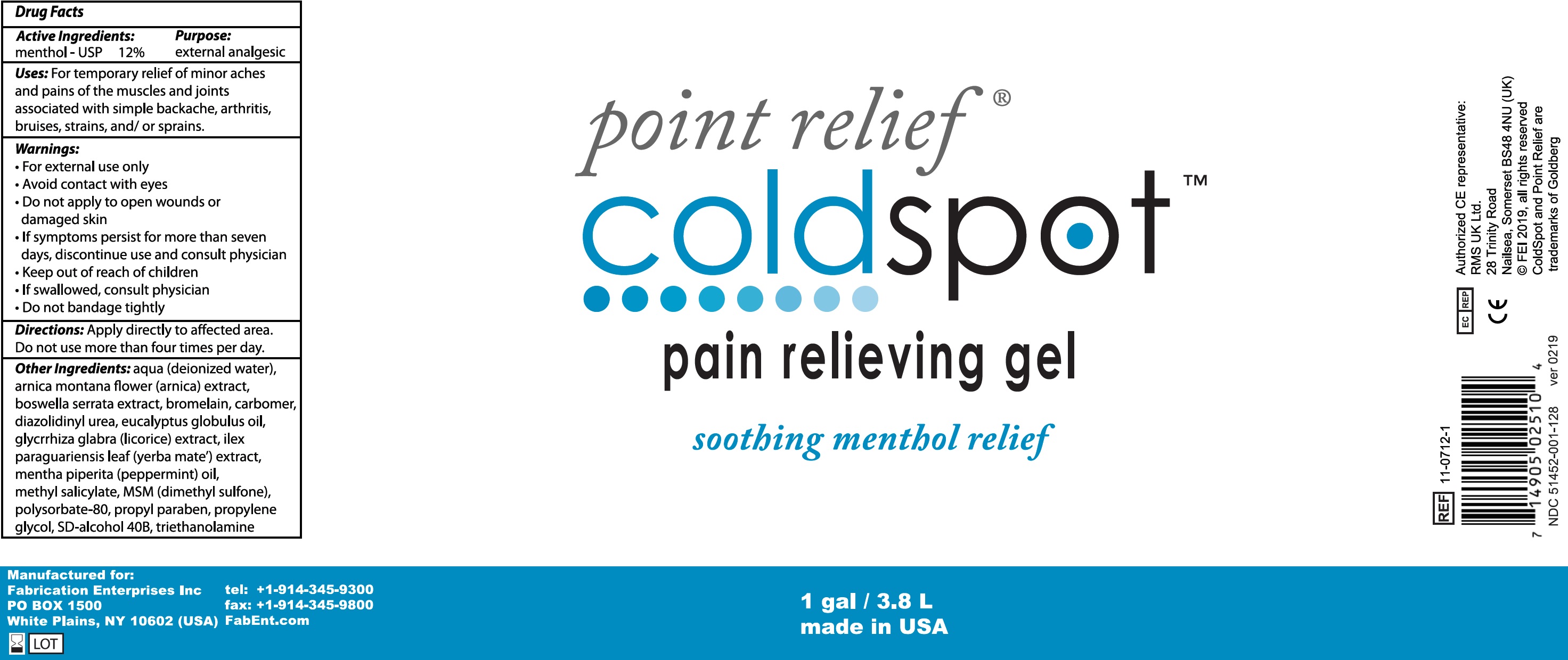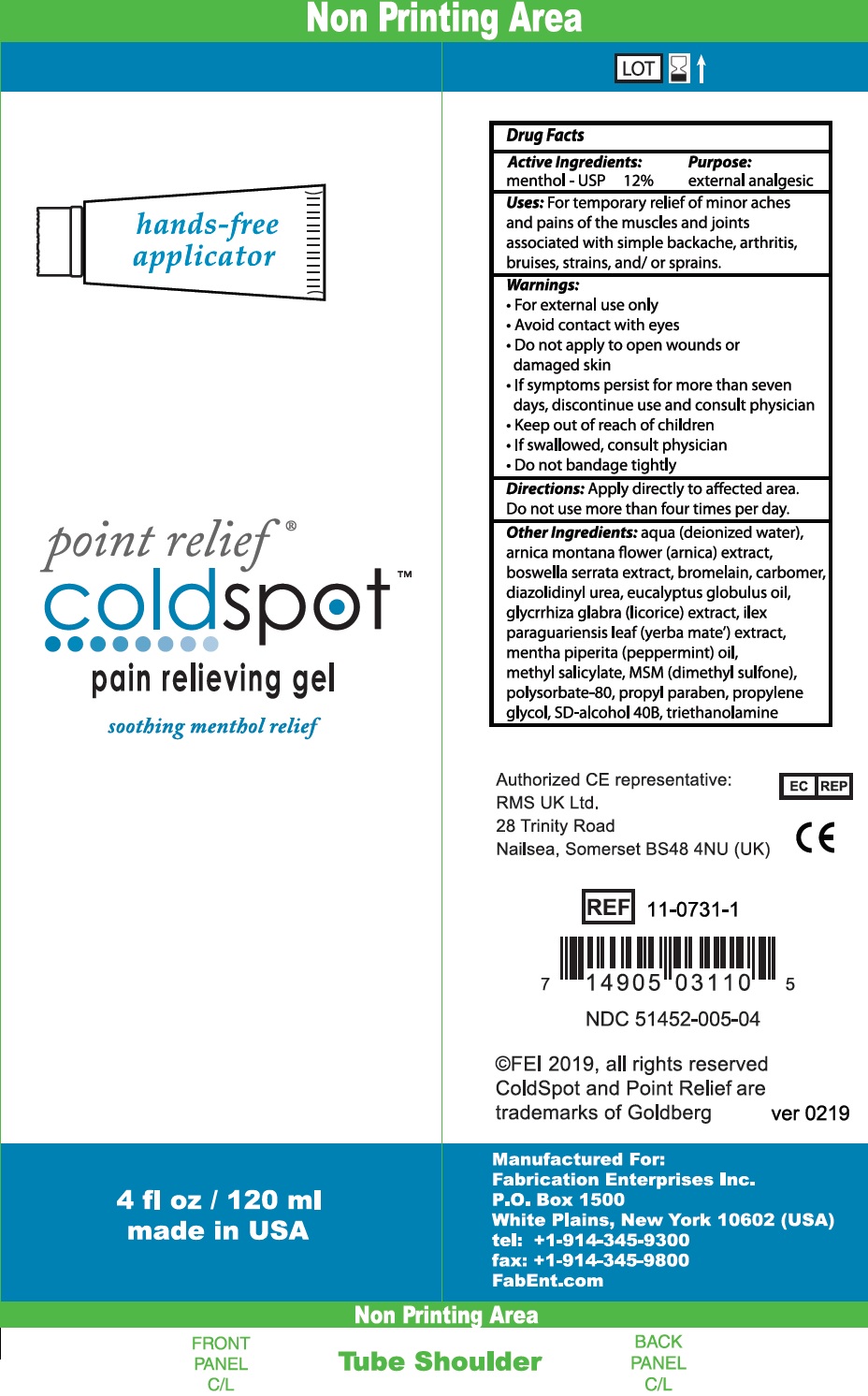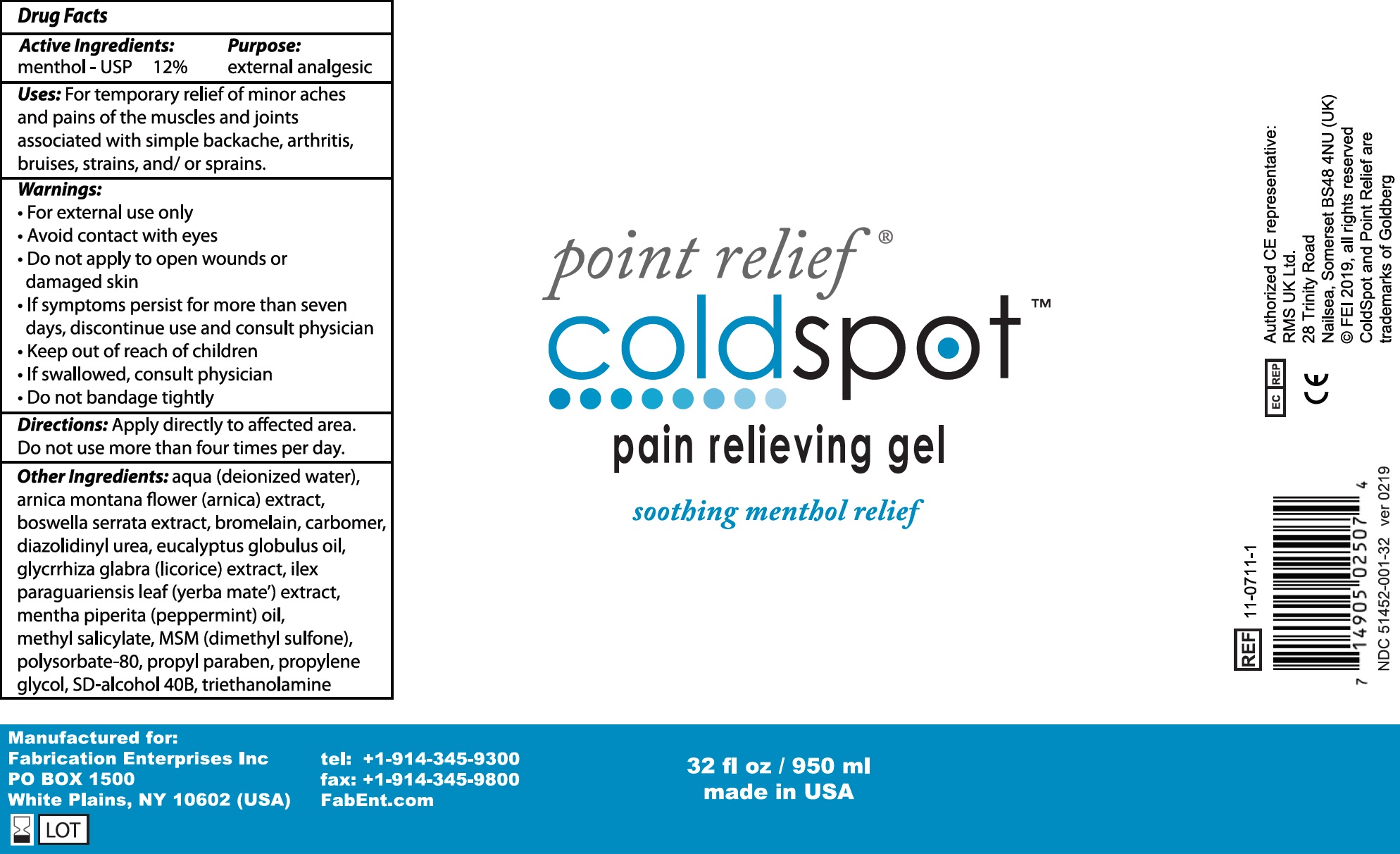 DRUG LABEL: Point Relief Cold Spot Pain Relieving
NDC: 51452-035 | Form: GEL
Manufacturer: Fabrication Enterprises
Category: otc | Type: HUMAN OTC DRUG LABEL
Date: 20240125

ACTIVE INGREDIENTS: MENTHOL 120 mg/1 mL
INACTIVE INGREDIENTS: WATER; ARNICA MONTANA FLOWER; INDIAN FRANKINCENSE; BROMELAINS; CARBOXYPOLYMETHYLENE; DIAZOLIDINYL UREA; EUCALYPTUS OIL; GLYCYRRHIZA GLABRA; ILEX PARAGUARIENSIS LEAF; PEPPERMINT OIL; METHYL SALICYLATE; DIMETHYL SULFONE; POLYSORBATE 80; PROPYLPARABEN; PROPYLENE GLYCOL; TROLAMINE

Point Relief Cold Spot Pain Relieving Gel

Active Ingredients:

menthol - USP 12%

Purpose:

external analgesic

Uses:

For temporary relief of minor aches and pains of the muscles and joints associated with simple backache, arthritis, bruises, strains, and/ or sprains.

Warnings:

- For external use only
- Avoid contact with eyes

Do not apply

- to open wounds or damaged skin
- If symptoms persist for more than sevan days, discontinue use and consult physician

Keep out of reach of children

- If swallowed, consult physician
- Do not bandage tightly

Directions:

Apply directly to affected area. Do not use more than four fimes per day.

Other Ingredients:

aqua (deionized water), arnica montana flower (arnica) extract, boswellia serrata extract, bromelain, carbomer, diazolidinyl urea, eucalyptus globulus oil, glycyrrhiza glabra (licorice) extract, ilex paraguariensis leaf (yerba mate) extract, mentha piperita (peppermint) oil, methyl salicylate, MSM (dimethyl sulfone), polysorbate-80, propyl paraben, propylene glycol, SD-alcohol 40B, triethanolamine